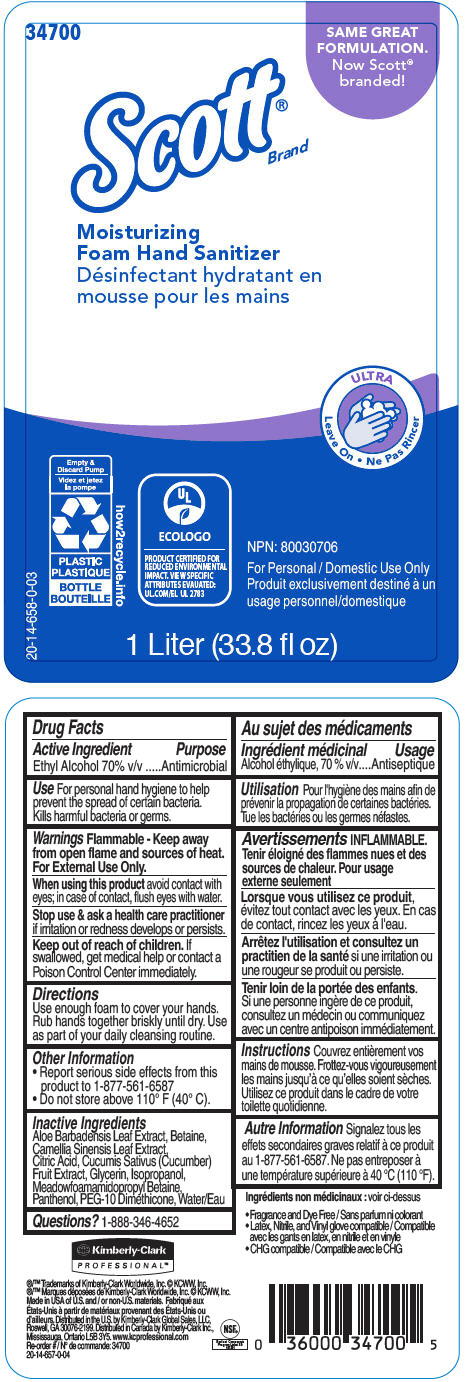 DRUG LABEL: Scott Moisturizing Foam Hand Sanitizer (Ultra)
NDC: 55118-532 | Form: SOLUTION
Manufacturer: Kimberly-Clark
Category: otc | Type: HUMAN OTC DRUG LABEL
Date: 20191018

ACTIVE INGREDIENTS: ALCOHOL 70 mL/100 mL
INACTIVE INGREDIENTS: ALOE VERA LEAF; Betaine; GREEN TEA LEAF; CITRIC ACID MONOHYDRATE; CUCUMBER; Glycerin; ISOPROPYL ALCOHOL; MEADOWFOAMAMIDOPROPYL BETAINE; Panthenol; PEG-10 DIMETHICONE (600 CST); Water

Scott® Moisturizing Foam Hand Sanitizer (Ultra)

Drug Facts

Active Ingredient

Ethyl Alcohol 70% v/v

Purpose

Antimicrobial

Use

For personal hand hygiene to help prevent the spread of certain bacteria. Kills harmful bacteria or germs.

Warnings

Flammable - Keep away from open flame and sources of heat.

For External Use Only.

When using this product avoid contact with eyes; in case of contact, flush eyes with water.

Stop use & ask a health care practitioner if irritation or redness develops or persists.

Keep out of reach of children. If swallowed, get medical help or contact a Poison Control Center immediately.

Directions

Use enough foam to cover your hands. Rub hands together briskly until dry. Use as part of your daily cleansing routine.

Other Information

- Report serious side effects from this product to 1-877-561-6587
- Do not store above 110° F (40° C).

Inactive Ingredients

Aloe Barbadensis Leaf Extract, Betaine, Camellia Sinensis Leaf Extract, Citric Acid, Cucumis Sativus (Cucumber) Fruit Extract, Glycerin, Isopropanol, Meadowfoamamidopropyl Betaine, Panthenol, PEG-10 Dimethicone, Water/Eau

Questions?

1-888-346-4652

Distributed in the U.S. by Kimberly-Clark Global Sales, LLC,
Roswell, GA 30076-2199. Distributed in Canada by Kimberly-Clark Inc.,
Mississauga, Ontario L5B 3Y5.

PRINCIPAL DISPLAY PANEL - 33.8 fl oz Bottle Label

34700

SAME GREAT
FORMULATION.
Now Scott®
branded!

Scott®
Brand

Moisturizing
Foam Hand Sanitizer

ULTRA
Leave On

Empty &
Discard Pump
PLASTIC
BOTTLE

20-14-658-0-03

how2recycle.info

ECOLOGO
PRODUCT CERTIFIED FOR
REDUCED ENVIRONMENTAL
IMPACT. VIEW SPECIFIC
ATTRIBUTES EVAUATED:
UL.COM/EL UL 2783

NPN: 80030706

For Personal / Domestic Use Only

1 Liter (33.8 fl oz)